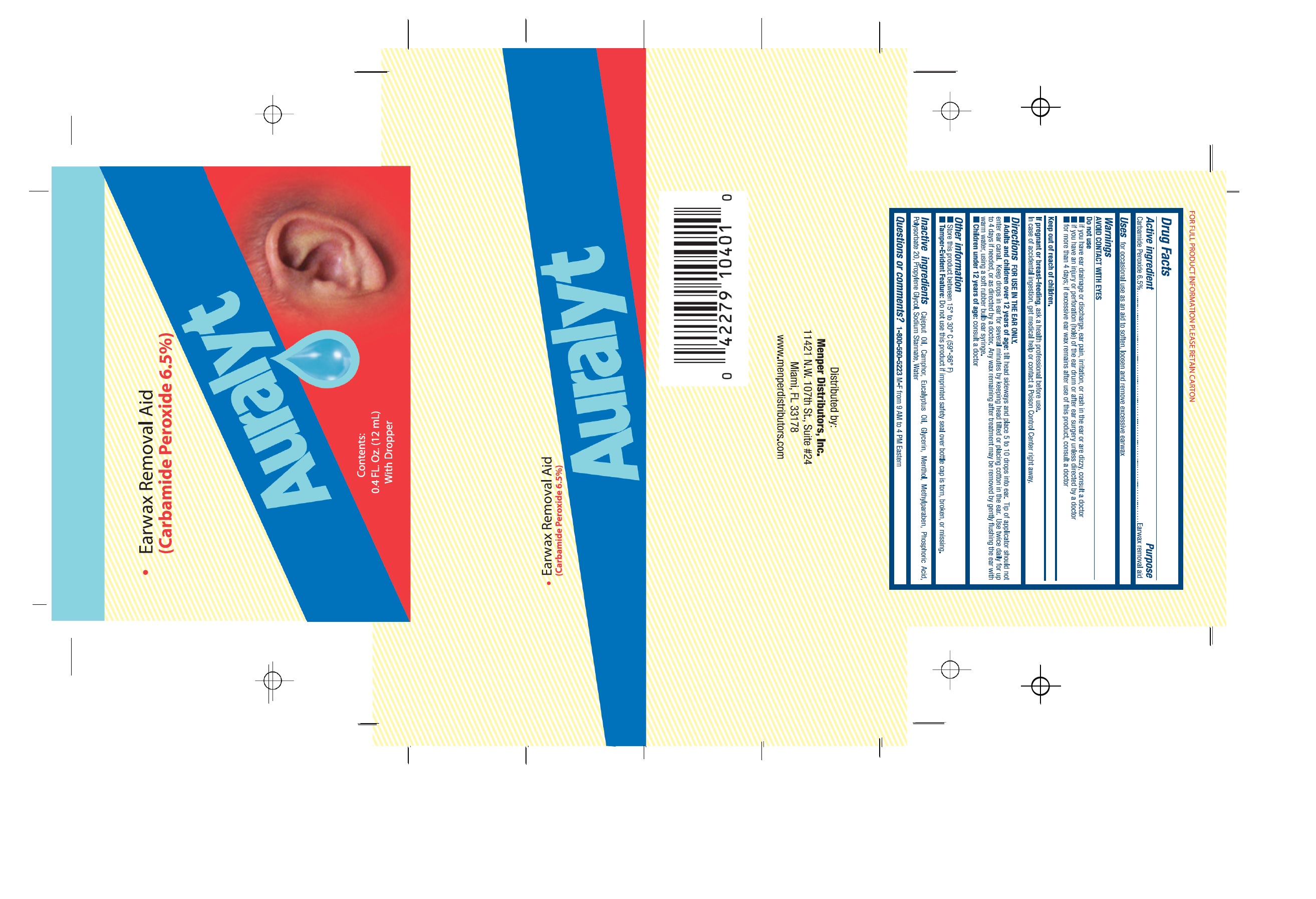 DRUG LABEL: Auralyt
NDC: 53145-311 | Form: LIQUID
Manufacturer: Menper Distributors, Inc
Category: otc | Type: HUMAN OTC DRUG LABEL
Date: 20250722

ACTIVE INGREDIENTS: CARBAMIDE PEROXIDE 7.8 mg/12 mL
INACTIVE INGREDIENTS: CAJUPUT OIL; CAMPHOR (NATURAL); EUCALYPTUS OIL; GLYCERIN; MENTHOL; METHYLPARABEN; PHOSPHORIC ACID; POLYSORBATE 20; PROPYLENE GLYCOL; SODIUM STANNATE; WATER

Auralyt

Active Ingredient

Carbamide Peroxide 6.5%...........Earwax removal aid

Purpose

Earwax removal aid

Uses

for occasional use as an aid to soften, loosen and remove excessive earwax

AVOID CONTACT WITH EYES

Do not use :

- if you have ear drainage or discharge, ear pain, irritation, or rash in the ear or are dizzy, consult a doctor
- if you have an injury or perforation (hole) of the ear drum or after ear surgery unless directed by a doctor
- for more than 4 days; if excessive ear wax remains after use of this product, consult a doctor.

keep out of reach of children.

if pregnate or breast-feeding

ask a health professional before use.

In case of accidental indegestion, get medical help or contact a Poison Control Center right away.

Directions FOR USE IN THE EAR ONLY.

- Adults and children over 12 years of age: Tilt head sideways and place 5 to 10 drops into ear. Tip of applicator should not enter ear canal. Keep drops in ear for several minutes by keeping head tilted or placing cotton in the ear. Use twice daily for up to 4 days if needed, or as directed by a doctor. Any wax remaining after treatment may be removed by gently flushing the ear with warm water, using soft ruber bulb ear syringe.
- Children under 12 years of age: consult a doctor.

Other information

Store this product between 15° to 30° C (59°-86° F)
Tamper-Evident Feature: Do not use this product if imprinted safety seal over bottle cap is torn, broken, or missing

Inactive ingredients

Cajeput oil, camphor, eucalyptus oil, glycerin, menthol, methlyparaben, phosphoric acid, polysorbate 20, propylene glycol, sodium stannate, water

Questions or comments?

1-800-560-5223 M-F from 9 AM to 4 PM Eastern.